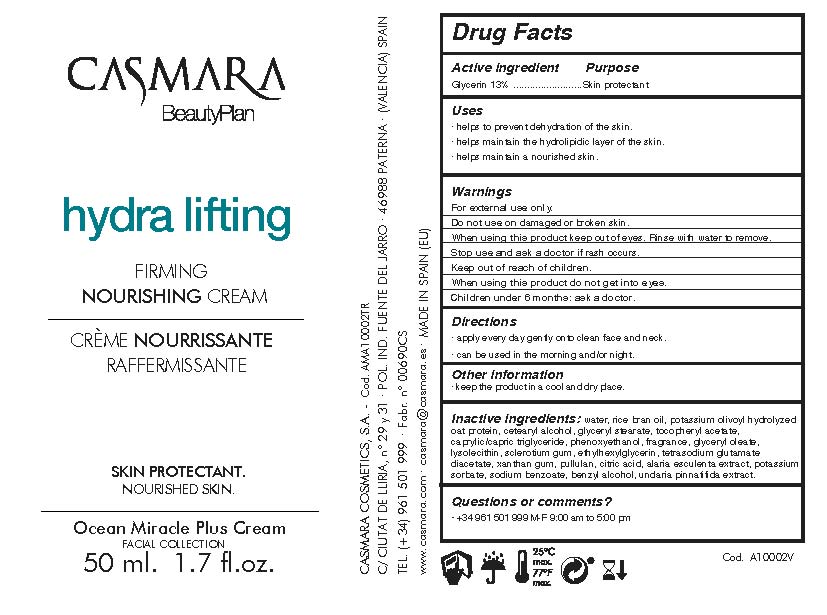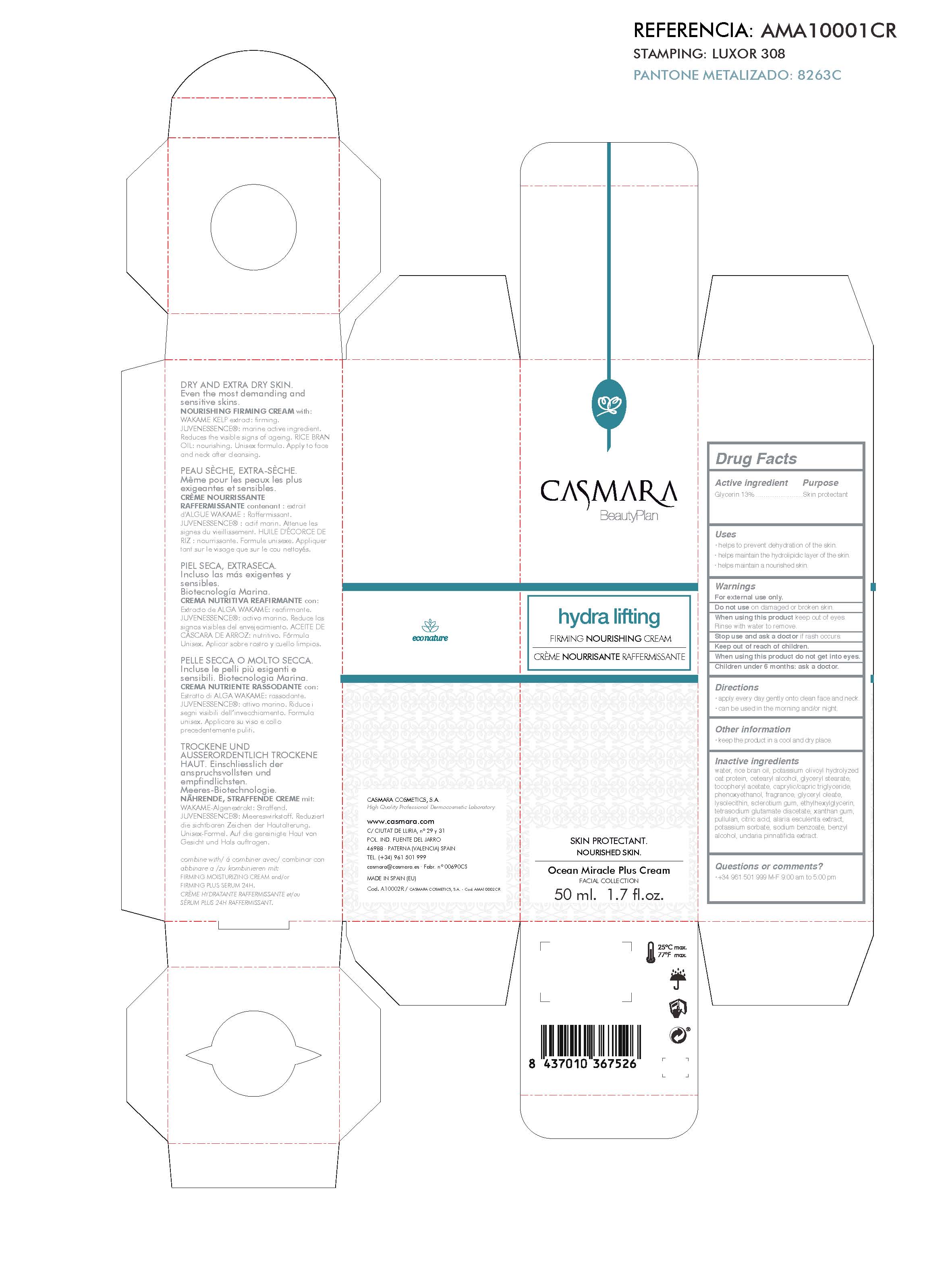 DRUG LABEL: Hydra lifting Firming Nourishing Cream
NDC: 20151-090 | Form: CREAM
Manufacturer: Casmara Cosmetics, SA
Category: otc | Type: HUMAN OTC DRUG LABEL
Date: 20170225

ACTIVE INGREDIENTS: GLYCERIN 13 mg/1 mL
INACTIVE INGREDIENTS: GLYCERYL STEARATE SE 1.05 mg/1 mL; RICE BRAN OIL 17 mg/1 mL; CITRIC ACID MONOHYDRATE 0.1 mg/1 mL; BETASIZOFIRAN 0.175 mg/1 mL; ALARIA ESCULENTA 0.05 mg/1 mL; ETHYLHEXYLGLYCERIN 0.1 mg/1 mL; WATER 62.376 mg/1 mL; XANTHAN GUM 0.075 mg/1 mL; PHENOXYETHANOL 0.9 mg/1 mL; GLYCERYL OLEATE 0.175 mg/1 mL; TETRASODIUM GLUTAMATE DIACETATE 0.094 mg/1 mL; SODIUM BENZOATE 0.035 mg/1 mL; POTASSIUM SORBATE 0.035 mg/1 mL; CETOSTEARYL ALCOHOL 1.05 mg/1 mL; PULLULAN 0.075 mg/1 mL; BENZYL ALCOHOL 0.035 mg/1 mL; OCTANOIC ACID 1-C-13 0.95 mg/1 mL; POTASSIUM HYDROLYZED JOJOBA ESTERS 1.05 mg/1 mL; .ALPHA.-TOCOPHEROL ACETATE 1 mg/1 mL; UNDARIA PINNATIFIDA 0.2 mg/1 mL; HYDROGENATED SOYBEAN LECITHIN 0.175 mg/1 mL

Hydra lifting Firming Nourishing Cream

ACTIVE INGREDIENTS PURPOSE

Glycerin 13%.................... Skin Protectant

Warnings

For external use only.

Do not use on damaged or broken skin.

When using this product keep our of the eyes. Rinse with water to remove.

Stop use and ask a doctor if rash occurs.

Keep out of reach of children.

Whhen using this product do not get into eyes.

Children under 6 months: as a doctor.

WARNINGS

Stop use and ask a doctor if rash occurs

Children under 6 months: ask a doctor

Warnings

Keep out of reach of children

Questions or comments?

+ 34 961 501 999 M-F 9:00 am to 5:00 pm

Other Information

. keep the product in a cool and dry place

Directions

. apply every day gently onto clean face and neck

. can be used in the morning and/or night

DOSAGE AND ADMINISTRATION

. apply every day gently onto clean dace and neck

. can be used in the morning and/or night

Uses

. helps to prevent dehydration of the skin.

. helps maintain the hydrolipidic layer of the skin

. helps to combat the signs of ageing

Inactive Ingredients

Potassium olivoyl hydrolyzed oat protein, Cetearyl alcohol, Glyceryl stearate, Tocopheryl acetate, Caprylic/capric triglyceride, Phenoxyethanol, Fragrance, Glyceryl oleate, Lysolecithin, Sclerotium gum, Ethylhexylglycerin, Tetrasodium glutamate diacetate,, Xanthan gum, Pullulan, Citric acid , Alaria esculenta extract, Potassium sorbate, Sodium benzoate, Benzyl alcohol, Undaria pinnatifida extract

Uses

. helps to prevent dehydration of the skin

. helps maintain the hydrolipidic layer of the skin

. helps to nourish the skin